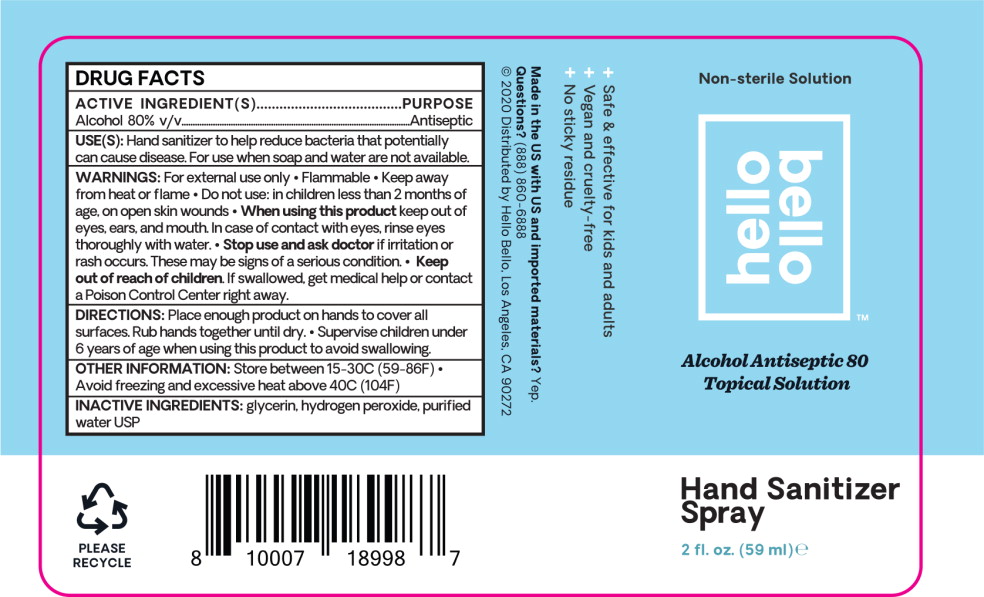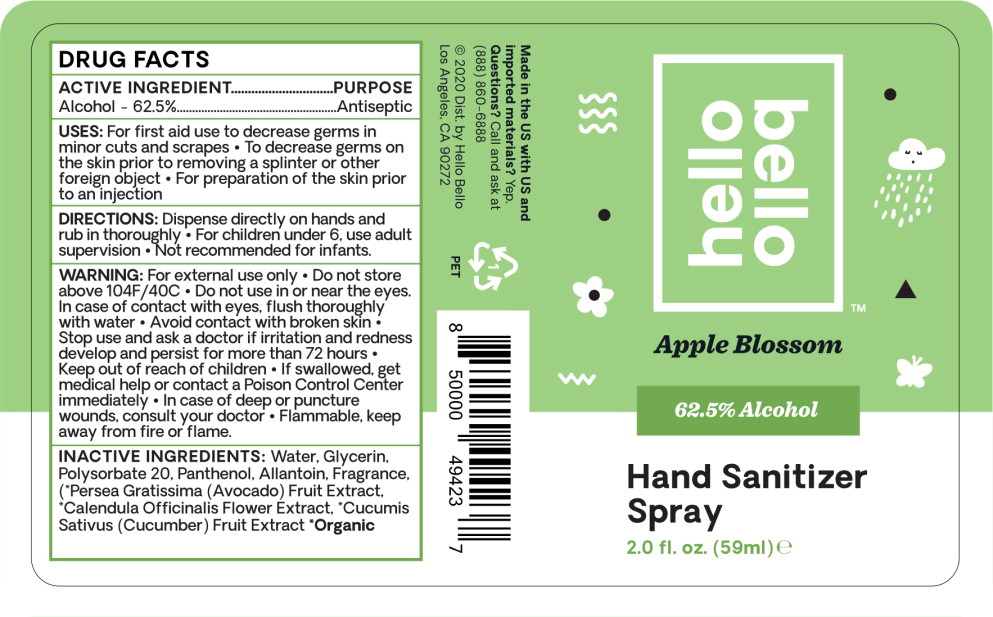 DRUG LABEL: Alcohol
NDC: 73418-042 | Form: SPRAY
Manufacturer: Hello Bello
Category: otc | Type: HUMAN OTC DRUG LABEL
Date: 20210209

ACTIVE INGREDIENTS: Alcohol 80 mL/100 mL
INACTIVE INGREDIENTS: Glycerin; Hydrogen Peroxide; Water

DRUG FACTS

ACTIVE INGREDIENT(S)

Alcohol 80% v/v.

PURPOSE

Antiseptic

USE(S):

Hand sanitizer to help reduce bacteria that potentially can cause disease. For use when soap and water are not available.

WARNINGS:

For external use only

- Flammable
- Keep away from heat or flame

- Do not use: in children less than 2 months of age, on open skin wounds

- When using this product keep out of eyes, ears, and mouth. In case of contact with eyes, rinse eyes thoroughly with water.

- Stop use and ask doctor if irritation or rash occurs. These may be signs of a serious condition.

- Keep out of reach of children. If swallowed, get medical help or contact a Poison Control Center right away.

DIRECTIONS:

Place enough product on hands to cover all surfaces. Rub hands together until dry.

- Supervise children under 6 years of age when using this product to avoid swallowing.

OTHER INFORMATION:

Store between 15-30C (59-86F)

- Avoid freezing and excessive heat above 40C (104F)

INACTIVE INGREDIENTS:

glycerin, hydrogen peroxide, purified water USP

Principal Display Panel – 59 mL Bottle Label

Non-sterile Solution

hello
bello™

Alcohol Antiseptic 80
Topical Solution

Hand Sanitizer
Spray

2 fl. oz. (59 ml) e

Principal Display Panel – 59 mL Bottle Label

hello
bello™

Apple Blossom

62.5% Alcohol

Hand Sanitizer
Spray

2.0 fl. oz. (59 ml) e